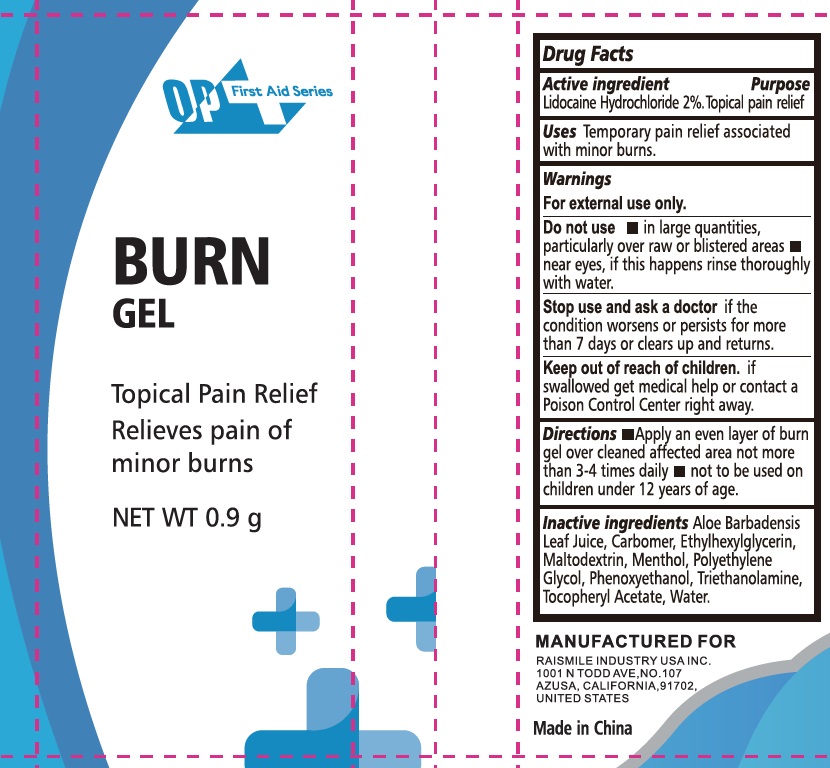 DRUG LABEL: PO First Aid Series BURN
NDC: 43473-062 | Form: GEL
Manufacturer: Nantong Health & Beyond Hygienic Products Inc.
Category: otc | Type: HUMAN OTC DRUG LABEL
Date: 20241205

ACTIVE INGREDIENTS: LIDOCAINE HYDROCHLORIDE 2 g/100 g
INACTIVE INGREDIENTS: WATER; ALOE VERA LEAF; CARBOMER 934; MENTHOL; ETHYLHEXYLGLYCERIN; MALTODEXTRIN; PHENOXYETHANOL; PROPYLENE GLYCOL; TRICLOSAN; .ALPHA.-TOCOPHEROL ACETATE

43473-062 PO First Aid Series Burn Gel

Active ingredient

Lidocaine HCI 2%

Purpose

Topical Pain Relief

Uses

Temporary relief of pain associated with minor burns.

Warnings

For external use only.

Do not use

■ in large quantities, particularly over raw or blistered areas

■ near eyes, if this happens rinse thoroughly with water

Stop use and ask a doctorif the condition worsens or persists for more than 7 days or clears up and returns

Keep out of reach of children. If swallowed, get medical help or contact a Poison Control Center right away

Directions

■ Apply an even layer of burn gel over deaned affected area not more than 3-4 times daily

■ not to be used on children under 12 years of age.

Inactive ingredients

Aloe Barbadensis Leaf Juice, Carbomer, Ethylhexgilglycerin, Maltodextrin, Menthol, Polyethylene Glycol, Phenoxyethanol, Triethanolamine, Tocopheryl Acetate, Water.